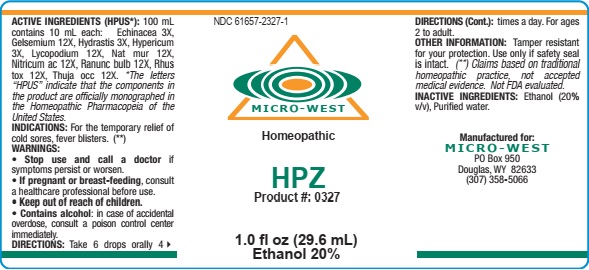 DRUG LABEL: HPZ
NDC: 61657-2327 | Form: LIQUID
Manufacturer: White Manufacturing Inc. DBA Micro-West
Category: homeopathic | Type: HUMAN OTC DRUG LABEL
Date: 20210121

ACTIVE INGREDIENTS: ECHINACEA PURPUREA 3 [hp_X]/30 mL; GELSEMIUM SEMPERVIRENS ROOT 12 [hp_X]/30 mL; GOLDENSEAL 3 [hp_X]/30 mL; ST. JOHN'S WORT 3 [hp_X]/30 mL; LYCOPODIUM CLAVATUM SPORE 12 [hp_X]/30 mL; SODIUM CHLORIDE 12 [hp_X]/30 mL; NITRIC ACID 12 [hp_X]/30 mL; RANUNCULUS BULBOSUS 12 [hp_X]/30 mL; TOXICODENDRON PUBESCENS LEAF 12 [hp_X]/30 mL; THUJA OCCIDENTALIS LEAFY TWIG 12 [hp_X]/30 mL
INACTIVE INGREDIENTS: ALCOHOL; WATER

HPZ

ACTIVE INGREDIENTS (HPUS*): 100 mL

contains 10 mL each: Echinacea 3X,

Gelsemium 12X, Hydrastis 3X, Hypericum

3X, Lycopodium 12X, Nat mur 12X,

Nitricum ac 12X, Ranunc bulb 12X, Rhus

tox 12X, Thuja occ 12X. * The letters

"HPUS" indicate that the components in

the product are officially monographed in

the Homeopathic Pharmacopoeia of the

United States.

INDICATIONS: For the temporary relief of

cold sores, fever blisters. (**)

WARNINGS:

• Stop use and call a doctor if

symptoms persist or worsen.

• If pregant or breast-feeding, consult

a healthcare professional before use.

• Keep out of reach of children.

• Contains alcohol: in case of accidental

overdose, consult a poison control center

immediately.

• Keep out of reach of children.

DOSAGE AND ADMINISTRATION

DIRECTIONS : Take 6 drops orally 4 times a day. For ages

2 to adult.

OTHER INFORMATION: Tamper resistant

for your protection. Use only if safety seal

is intact. (**) Claims base on traditional

homeopathic practice, not accepted

medical evidence. Not FDA evaluated.

INACTIVE INGREDIENTS: Ethanol (20%)

v/v), Purified water.

QUESTIONS

Manufactured for:

MICRO-WEST

PO Box 950

Douglas, WY 82633

(307)358-5066

PACKAGE LABEL

NDC 61657-2327-1

MICRO-WEST

Homeopathic

HPZ

Product #: 0327

1.0 fl oz (29.6 mL)

Ethanol 20%

PURPOSE

For the temporary relief of

cold sores, fever blisters. (**)